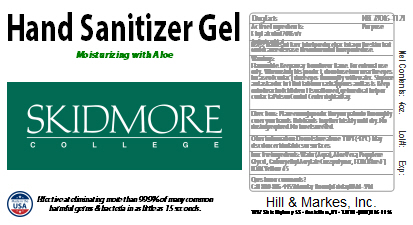 DRUG LABEL: Hand Sanitizer
NDC: 78046-1121 | Form: SOLUTION
Manufacturer: Hill & Markes
Category: otc | Type: HUMAN OTC DRUG LABEL
Date: 20200817

ACTIVE INGREDIENTS: ALCOHOL 0.7 mL/1 mL
INACTIVE INGREDIENTS: PROPYLENE GLYCOL; ALOE VERA LEAF; WATER; AMMONIUM ACRYLOYLDIMETHYLTAURATE; FD&C BLUE NO. 1; FD&C YELLOW NO. 5

Active Ingredient(s)

Alcohol 70% v/v. Purpose: Antimicrobial

Purpose

Antiseptic, Hand Sanitizer

Use

Hand sanitizer to help reduce bacteria on the skin that could cause disease. Recommended for repeated use.

Warnings

For external use only. Flammable. Keep away from heat or flame

When using this product keep out of eyes, ears, and mouth. In case of contact with eyes, rinse eyes thoroughly with water.

Stop use and ask a doctor if irritation or rash appears and lasts.

Keep out of reach of children. If swallowed, get medical help or contact a Poison Control Center right away.

Directions

- Place enough product in your palm to thoroughly cover your hands Rub hands together briskly until dry.
  No rinsing required. No towels needed.

Inactive ingredients

Water (Aqua), Aloe Vera, Propylene Glycol, Carboxethyl Acrylate Crosspolymer, FD&C Blue #1, FD&C Yellow #5

DESCRIPTION

Hand Sanitizer Gel

Moisturizing with Aloe

Effective at eliminating more than 99.9% of many common harmful germs & bacteria in as little as 15 seconds.

Package Label - Principal Display Panel

118.29 mL NDC: 78046-1121 -1